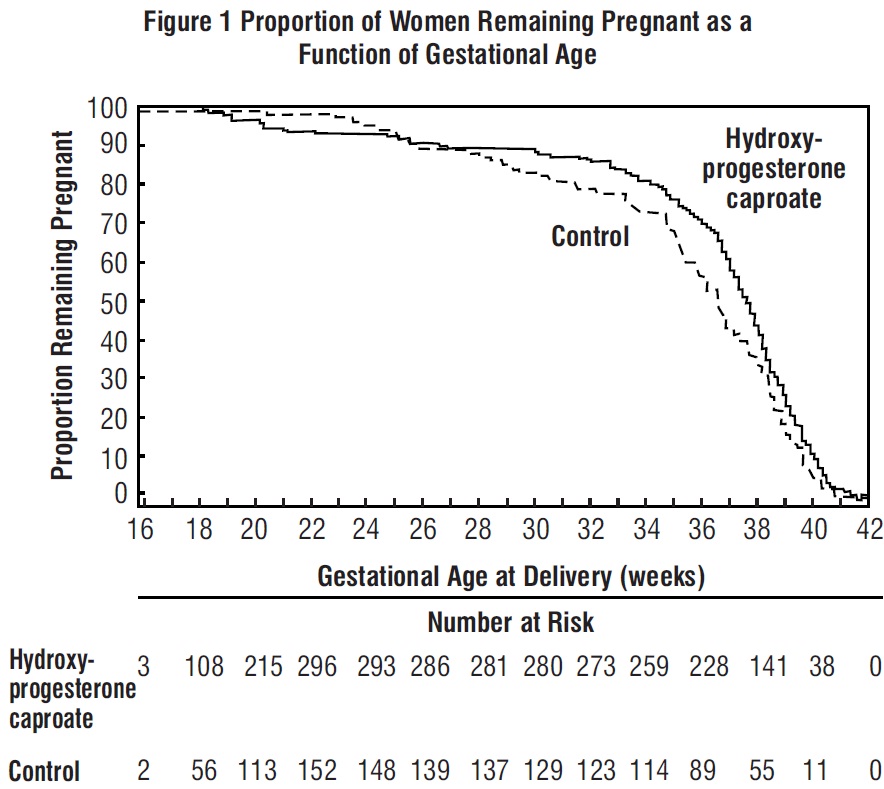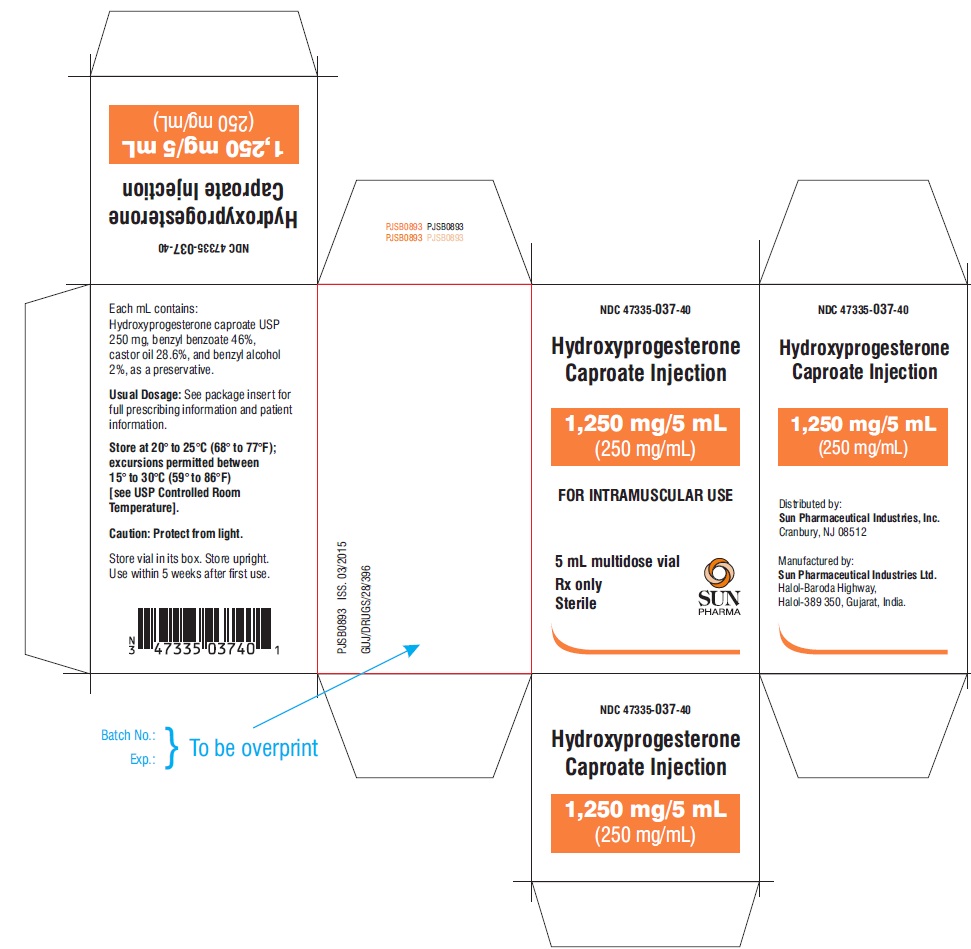 DRUG LABEL: HYDROXYPROGESTERONE CAPROATE
NDC: 47335-037 | Form: INJECTION
Manufacturer: Sun Pharmaceutical Industries, Inc.
Category: prescription | Type: Human Prescription Drug Label
Date: 20190418

ACTIVE INGREDIENTS: HYDROXYPROGESTERONE CAPROATE 250 mg/1 mL
INACTIVE INGREDIENTS: BENZYL ALCOHOL; BENZYL BENZOATE; CASTOR OIL

HIGHLIGHTS OF PRESCRIBING INFORMATION

These highlights do not include all the information needed to use HYDROXYPROGESTERONE CAPROATE INJECTION safely and effectively. See full prescribing information for HYDROXYPROGESTERONE CAPROATE INJECTION.
HYDROXYPROGESTERONE CAPROATE injection, for intramuscular use.
Initial U.S. Approval: 1956

RECENT MAJOR CHANGES

Dosage and Administration, Dosing (2.1) 02/2018

Dosage and Administration, Preparation & Administration (2.2) 02/2018

1 INDICATIONS AND USAGE

Hydroxyprogesterone caproate is a progestin indicated to reduce the risk of preterm birth in women with a singleton pregnancy who have a history of singleton spontaneous preterm birth (1). The effectiveness of hydroxyprogesterone caproate is based on improvement in the proportion of women who delivered < 37 weeks of gestation (14). There are no controlled trials demonstrating a direct clinical benefit, such as improvement in neonatal mortality and morbidity.

Limitation of use: Hydroxyprogesterone caproate injection is not intended for use in women with multiple gestations or other risk factors for preterm birth. (1)

2 DOSAGE AND ADMINISTRATION

- Hydroxyprogesterone caproate injection (Multi-dose vials): Administer intramuscularly at a dose of 250 mg (1 mL) once weekly in the upper outer quadrant of the gluteus maximus (2.1)
- Begin treatment between 16 weeks, 0 days and 20 weeks, 6 days of gestation (2.1)
- Continue administration once weekly until week 37 (through 36 weeks, 6 days) of gestation or delivery, whichever occurs first (2.1)

3 DOSAGE FORMS AND STRENGTHS

5 mL multi-dose vial for intramuscular use contains 1250 mg of hydroxyprogesterone caproate (250 mg/mL). (3)

4 CONTRAINDICATIONS

- Current or history of thrombosis or thromboembolic disorders (4)
- Known or suspected breast cancer, other hormone-sensitive cancer, or history of these conditions (4)
- Undiagnosed abnormal vaginal bleeding unrelated to pregnancy (4)
- Cholestatic jaundice of pregnancy (4)
- Liver tumors, benign or malignant, or active liver disease (4)
- Uncontrolled hypertension (4)

5 WARNINGS AND PRECAUTIONS

- Thromboembolic disorders: Discontinue if thrombosis or thromboembolism occurs (5.1)
- Allergic reactions: Consider discontinuing if allergic reactions occur (5.2)
- Decreased glucose tolerance: Monitor prediabetic and diabetic women receiving hydroxyprogesterone caproate (5.3)
- Fluid retention: Monitor women with conditions that may be affected by fluid retention, such as preeclampsia, epilepsy, cardiac or renal dysfunction (5.4)
- Depression: Monitor women with a history of clinical depression; discontinue hydroxyprogesterone caproate if depression recurs (5.5)

6 ADVERSE REACTIONS

- In a study where the hydroxyprogesterone caproate intramuscular injection was compared with placebo, the most common adverse reactions reported with hydroxyprogesterone caproate intramuscular injection (reported incidence in ≥ 2% of subjects and higher than in the control group) were: injection site reactions (pain [35%], swelling [17%], pruritus [6%], nodule [5%]), urticaria (12%), pruritus (8%), nausea (6%), and diarrhea (2%). (6.1)

To report SUSPECTED ADVERSE REACTIONS, contact Sun Pharmaceutical Industries, Inc. at 1-800-818-4555 or FDA at 1-800-FDA-1088 or www.fda.gov/medwatch.

FULL PRESCRIBING INFORMATION

1 INDICATIONS AND USAGE

Hydroxyprogesterone caproate is a progestin indicated to reduce the risk of preterm birth in women with a singleton pregnancy who have a history of singleton spontaneous preterm birth. The effectiveness of hydroxyprogesterone caproate injection is based on improvement in the proportion of women who delivered < 37 weeks of gestation. There are no controlled trials demonstrating a direct clinical benefit, such as improvement in neonatal mortality and morbidity.
Limitation of use: While there are many risk factors for preterm birth, safety and efficacy of hydroxyprogesterone caproate injection has been demonstrated only in women with a prior spontaneous singleton preterm birth. It is not intended for use in women with multiple gestations or other risk factors for preterm birth.

2 DOSAGE AND ADMINISTRATION

2.1 Dosing

- Hydroxyprogesterone caproate injection (Multi-dose vials): Administer intramuscularly at a dose of 250 mg (1 mL) once weekly (every 7 days) in the upper outer quadrant of the gluteus maximus by a healthcare provider
- Begin treatment between 16 weeks, 0 days and 20 weeks, 6 days of gestation
- Continue administration once weekly until week 37 (through 36 weeks, 6 days) of gestation or delivery, whichever occurs first

2.2 Preparation and Administration

Parenteral drug products should be inspected visually for particulate matter and discoloration prior to administration, whenever solution and container permit. Hydroxyprogesterone caproate injection is a clear, yellow solution. The solution must be clear at the time of use; replace vial if visible particles or crystals are present.

Specific instructions for administration by dosage form:

Hydroxyprogesterone caproate injection multi-dose vials (intramuscular use only)

Hydroxyprogesterone caproate injection multi-dose vials are only for intramuscular injection with a syringe into the upper outer quadrant of the gluteus maximus, rotating the injection site to the alternate side from the previous week, using the following preparation and administration procedure:

1. Clean the vial top with an alcohol swab before use.
2. Draw up 1 mL of drug into a 3 mL syringe with an 18 gauge needle.
3. Change the needle to a 21 gauge 1½ inch needle.
4. After preparing the skin, inject in the upper outer quadrant of the gluteus maximus. The solution is viscous and oily. Slow injection (over one minute or longer) is recommended.
5. Applying pressure to the injection site may minimize bruising and swelling.

If the 5 mL multi-dose vial is used, discard any unused product 5 weeks after first use.

3 DOSAGE FORMS AND STRENGTHS

Intramuscular injection: 1250 mg/5 mL (250 mg/mL) clear yellow solution in multiple-dose vials.

4 CONTRAINDICATIONS

Do not use hydroxyprogesterone caproate injection in women with any of the following conditions:

- Current or history of thrombosis or thromboembolic disorders
- Known or suspected breast cancer, other hormone-sensitive cancer, or history of these conditions
- Undiagnosed abnormal vaginal bleeding unrelated to pregnancy
- Cholestatic jaundice of pregnancy
- Liver tumors, benign or malignant, or active liver disease
- Uncontrolled hypertension

5 WARNINGS AND PRECAUTIONS

5.1 Thromboembolic Disorders

Discontinue hydroxyprogesterone caproate injection if an arterial or deep venous thrombotic or thromboembolic event occurs.

5.2 Allergic Reactions

Allergic reactions, including urticaria, pruritus and angioedema, have been reported with use of hydroxyprogesterone caproate injection or with other products containing castor oil. Consider discontinuing the drug if such reactions occur.

5.3 Decrease in Glucose Tolerance

A decrease in glucose tolerance has been observed in some patients on progestin treatment. The mechanism of this decrease is not known. Carefully monitor prediabetic and diabetic women while they are receiving hydroxyprogesterone caproate injection.

5.4 Fluid Retention

Because progestational drugs may cause some degree of fluid retention, carefully monitor women with conditions that might be influenced by this effect (e.g., preeclampsia, epilepsy, migraine, asthma, cardiac or renal dysfunction).

5.5 Depression

Monitor women who have a history of clinical depression and discontinue hydroxyprogesterone caproate injection if clinical depression recurs.

5.6 Jaundice

Carefully monitor women who develop jaundice while receiving hydroxyprogesterone caproate injection and consider whether the benefit of use warrants continuation.

5.7 Hypertension

Carefully monitor women who develop hypertension while receiving hydroxyprogesterone caproate injection and consider whether the benefit of use warrants continuation.

6 ADVERSE REACTIONS

For the most serious adverse reactions to the use of progestins, see Warnings and Precautions (5).

6.1 Clinical Trials Experience

Because clinical trials are conducted under widely varying conditions, adverse reaction rates observed in the clinical trials of a drug cannot be directly compared to the rates in the clinical trials of another drug and may not reflect the rates observed in practice.

In a vehicle (placebo)-controlled clinical trial of 463 pregnant women at risk for spontaneous preterm delivery based on obstetrical history, 310 received 250 mg of hydroxyprogesterone caproate injection and 153 received a vehicle formulation containing no drug by a weekly intramuscular injection beginning at 16 to 20 weeks of gestation and continuing until 37 weeks of gestation or delivery, whichever occurred first. [See Clinical Studies (14.1).]

Certain pregnancy-related fetal and maternal complications or events were numerically increased in the hydroxyprogesterone caproate injection-treated subjects as compared to control subjects, including miscarriage and stillbirth, admission for preterm labor, preeclampsia or gestational hypertension, gestational diabetes, and oligohydramnios (Tables 1 and 2).
Table 1 Selected Fetal Complications

Pregnancy Complication | Hydroxyprogesterone Caproate Injection n/N | Control n/N
Miscarriage (< 20 weeks)^1 | 5/209 | 0/107
Stillbirth (≥ 20 weeks)^2 | 6/305 | 2/153

^1 N = Total number of subjects enrolled prior to 20 weeks 0 days

^2 N = Total number of subjects at risk ≥ 20 weeks
Table 2 Selected Maternal Complications

Pregnancy Complication | Hydroxyprogesterone Caproate Injection N= 310 % | Control N= 153 %
Admission for preterm labor^1 | 16.0 | 13.8
Preeclamps ia or gestation al hypertension | 8.8 | 4.6
Gestational diabetes | 5.6 | 4.6
Oligohydramnios | 3.6 | 1.3

^1 Other than delivery admission.

Common Adverse Reactions:

The most common adverse reaction with intramuscular injection was injection site pain, which was reported after at least one injection by 34.8% of the hydroxyprogesterone caproate injection group and 32.7% of the control group. Table 3 lists adverse reactions that occurred in ≥ 2% of subjects and at a higher rate in the hydroxyprogesterone caproate injection group than in the control group.
Table 3 Adverse Reactions Occurring in ≥ 2% of Hydroxyprogesterone Caproate Injection-Treated Subjects and at a Higher Rate than Control Subjects

Preferred Term | Hydroxyprogesterone Caproate Injection N=310 % | Control N=153 %
Injection site pain | 34.8 | 32.7
Injection site swelling | 17.1 | 7.8
Urticaria | 12.3 | 11.1
Pruritus | 7.7 | 5.9
Injection site pruritus | 5.8 | 3.3
Nausea | 5.8 | 4.6
Injection site nodule | 4.5 | 2.0
Diarrhea | 2.3 | 0.7

In the clinical trial using intramuscular injection, 2.2% of subjects receiving hydroxyprogesterone caproate injection were reported as discontinuing therapy due to adverse reactions compared to 2.6% of control subjects. The most common adverse reactions that led to discontinuation in both groups were urticaria and injection site pain/swelling (1% each).

Pulmonary embolus in one subject and injection site cellulitis in another subject were reported as serious adverse reactions in hydroxyprogesterone caproate injection-treated subjects.

6.2 Postmarketing Experience

The following adverse reactions have been identified during postapproval use of hydroxyprogesterone caproate injection. Because these reactions are reported voluntarily from a population of uncertain size, it is not always possible to reliably estimate their frequency or establish a causal relationship to drug exposure.

- Body as a whole: Local injection site reactions (including erythema, urticaria, rash, irritation, hypersensitivity, warmth); fatigue; fever; hot flashes/flushes
- Digestive disorders: Vomiting
- Infections: Urinary tract infection
- Nervous system disorders: Headache, dizziness
- Pregnancy, puerperium and perinatal conditions: Cervical incompetence, premature rupture of membranes
- Reproductive system and breast disorders: Cervical dilation, shortened cervix
- Respiratory disorders: Dyspnea, chest discomfort
- Skin: Rash

7 DRUG INTERACTIONS

In vitro drug-drug interaction studies were conducted with hydroxyprogesterone caproate injection. Hydroxyprogesterone caproate has minimal potential for CYP1A2, CYP2A6, and CYP2B6 related drug-drug interactions at the clinically relevant concentrations. In vitro data indicated that therapeutic concentration of hydroxyprogesterone caproate is not likely to inhibit the activity of CYP2C8, CYP2C9, CYP2C19, CYP2D6, CYP2E1, and CYP3A4 [See Clinical Pharmacology (12.3).] No in vivo drug-drug interaction studies were conducted with hydroxyprogesterone caproate injection.

8 USE IN SPECIFIC POPULATIONS

8.1 Pregnancy

Risk Summary

Hydroxyprogesterone caproate injection is indicated to reduce the risk of preterm birth in women with a singleton pregnancy who have a history of singleton spontaneous preterm birth. Fetal, neonatal, and maternal risks are discussed throughout labeling. Data from the placebo-controlled clinical trial and the infant follow-up safety study [see Clinical Studies (14.1, 14.2)] did not show a difference in adverse developmental outcomes between children of hydroxyprogesterone caproate injection-treated women and children of control subjects. However, these data are insufficient to determine a drug-associated risk of adverse developmental outcomes as none of the hydroxyprogesterone caproate injection-treated women received the drug during the first trimester of pregnancy. In animal reproduction studies, intramuscular administration of hydroxyprogesterone caproate to pregnant rats during gestation at doses 5 times the human dose equivalent based on a 60-kg human was not associated with adverse developmental outcomes.

In the U.S. general population, the estimated background risk of major birth defects and miscarriage in clinically recognized pregnancies is 2% to 4% and 15% to 20%, respectively.

Data

Animal Data

Reproduction studies of hydroxyprogesterone caproate administered to various animal species have been reported in the literature. In nonhuman primates, embryolethality was reported in rhesus monkeys administered hydroxyprogesterone caproate up to 2.4 and 24 times the human dose equivalent, but not in cynomolgus monkeys administered hydroxyprogesterone caproate at doses up to 2.4 times the human dose equivalent, every 7 days between days 20 and 146 of gestation. There were no teratogenic effects in either strain of monkey.

Reproduction studies have been performed in mice and rats at doses up to 95 and 5, respectively, times the human dose and have revealed no evidence of impaired fertility or harm to the fetus due to hydroxyprogesterone caproate.

8.2 Lactation

Risk Summary

Low levels of progestins are present in human milk with the use of progestin-containing products, including hydroxyprogesterone caproate. Published studies have reported no adverse effects of progestins on the breastfed child or on milk production.

8.4 Pediatric Use

Hydroxyprogesterone caproate injection is not indicated for use in women under 16 years of age. Safety and effectiveness in patients less than 16 years of age have not been established. A small number of women under age 18 years were studied; safety and efficacy are expected to be the same in women aged 16 years and above as for users 18 years and older [see Clinical Studies (14)].

8.6 Hepatic Impairment

No studies have been conducted to examine the pharmacokinetics of hydroxyprogesterone caproate injection in patients with hepatic impairment. Hydroxyprogesterone caproate injection is extensively metabolized and hepatic impairment may reduce the elimination of hydroxyprogesterone caproate injection.

10 OVERDOSAGE

There have been no reports of adverse events associated with overdosage of hydroxyprogesterone caproate injection in clinical trials. In the case of overdosage, the patient should be treated symptomatically.

11 DESCRIPTION

The active pharmaceutical ingredient in hydroxyprogesterone caproate injection USP is hydroxyprogesterone caproate, a progestin.

The chemical name for hydroxyprogesterone caproate is pregn-4-ene-3,20-dione,17[(1-oxohexyl)oxy]. It has a molecular formula of C27H40O4 and a molecular weight of 428.60. Hydroxyprogesterone caproate exists as white or creamy white crystalline powder with a melting point of 120° to 124°C.

The structural formula is:

Hydroxyprogesterone caproate injection USP is a clear, yellow, sterile, non-pyrogenic solution for intramuscular injection. Each 5 mL multi-dose vial contains hydroxyprogesterone caproate USP, 250 mg/mL (25% w/v), in castor oil (28.6% v/v) and benzyl benzoate (46% v/v) with the preservative benzyl alcohol (2% v/v).

12 CLINICAL PHARMACOLOGY

12.1 Mechanism of Action

Hydroxyprogesterone caproate is a synthetic progestin. The mechanism by which hydroxyprogesterone caproate reduces the risk of recurrent preterm birth is not known.

12.2 Pharmacodynamics

No specific pharmacodynamic studies were conducted with hydroxyprogesterone caproate injection.

12.3 Pharmacokinetics

Absorption: Female patients with a singleton pregnancy received intramuscular doses of 250 mg hydroxyprogesterone caproate for the reduction of preterm birth starting between 16 weeks 0 days and 20 weeks 6 days. All patients had blood drawn daily for 7 days to evaluate pharmacokinetics.

Table 4 Summary of Mean (Standard Deviation) Pharmacokinetic Parameters for Hydroxyprogesterone Caproate

Group (N) | Cmax (ng/mL) | Tmax (days)a | AUC(o-t)b (ng·hr/mL)
Group 1 (N=6) | 5.0 (1.5) | 5.5 (2.0-7.0) | 571.4 (195.2)
Group 2 (N=8) | 12.5 (3.9) | 1.0 (0.9-1.9) | 1269.6 (285.0)
Group 3 (N=11) | 12.3 (4.9) | 2.0 (1.0-3.0) | 1268.0 (511.6)

Blood was drawn daily for 7 days (1) starting 24 hours after the first dose between Weeks 16-20 (Group 1), (2) after a dose between Weeks 24-28 (Group 2), or (3) after a dose between Weeks 32-36 (Group 3)

a Reported as median (range)

b t = 7 days

For all three groups, peak concentration (Cmax) and area under the curve (AUC(1-7 days)) of the mono-hydroxylated metabolites were approximately 3-8-fold lower than the respective parameters for the parent drug, hydroxyprogesterone caproate. While di-hydroxylated and trihydroxylated metabolites were also detected in human plasma to a lesser extent, no meaningful quantitative results could be derived due to the absence of reference standards for these multiple hydroxylated metabolites. The relative activity and significance of these metabolites are not known.

The elimination half-life of hydroxyprogesterone caproate, as evaluated from 4 patients in the study who reached full-term in their pregnancies, was 16.4 (±3.6) days. The elimination half-life of the mono-hydroxylated metabolites was 19.7 (±6.2) days.

Distribution: Hydroxyprogesterone caproate binds extensively to plasma proteins including albumin and corticosteroid binding globulins.

Metabolism: In vitro studies have shown that hydroxyprogesterone caproate can be metabolized by human hepatocytes, both by phase I and phase II reactions. Hydroxyprogesterone caproate undergoes extensive reduction, hydroxylation and conjugation. The conjugated metabolites include sulfated, glucuronidated and acetylated products. In vitro data indicate that the metabolism of hydroxyprogesterone caproate is predominantly mediated by CYP3A4 and CYP3A5. The in vitro data indicate that the caproate group is retained during metabolism of hydroxyprogesterone caproate.

Excretion: Both conjugated metabolites and free steroids are excreted in the urine and feces, with the conjugated metabolites being prominent. Following intramuscular administration to pregnant women at 10 to 12 weeks gestation, approximately 50% of a dose was recovered in the feces and approximately 30% recovered in the urine.

Drug Interactions

Cytochrome P450 (CYP) enzymes: An in vitro inhibition study using human liver microsomes and CYP isoform-selective substrates indicated that hydroxyprogesterone caproate increased the metabolic rate of CYP1A2, CYP2A6, and CYP2B6 by approximately 80%, 150%, and 80%, respectively. However, in another in vitro study using human hepatocytes under conditions where the prototypical inducers or inhibitors caused the anticipated increases or decreases in CYP enzyme activities, hydroxyprogesterone caproate did not induce or inhibit CYP1A2, CYP2A6, or CYP2B6 activity. Overall, the findings indicate that hydroxyprogesterone caproate has minimal potential for CYP1A2, CYP2A6, and CYP2B6 related drug-drug interactions at the clinically relevant concentrations.

In vitro data indicated that therapeutic concentration of hydroxyprogesterone caproate is not likely to inhibit the activity of CYP2C8, CYP2C9, CYP2C19, CYP2D6, CYP2E1, and CYP3A4.

13 NONCLINICAL TOXICOLOGY

13.1 Carcinogenesis, Mutagenesis, Impairment of Fertility

Hydroxyprogesterone caproate has not been adequately evaluated for carcinogenicity.

No reproductive or developmental toxicity or impaired fertility was observed in a multigenerational study in rats. Hydroxyprogesterone caproate administered intramuscularly, at gestational exposures up to 5 times the recommended human dose, had no adverse effects on the parental (F0) dams, their developing offspring (F1), or the latter offspring's ability to produce a viable, normal second (F2) generation.

14 CLINICAL STUDIES

14.1 Clinical Trial to Evaluate Reduction of Risk of Preterm Birth

In a multicenter, randomized, double-blind, vehicle (placebo)-controlled clinical trial, the safety and effectiveness of hydroxyprogesterone caproate injection for the reduction of the risk of spontaneous preterm birth was studied in women with a singleton pregnancy (age 16 to 43 years) who had a documented history of singleton spontaneous preterm birth (defined as delivery at less than 37 weeks of gestation following spontaneous preterm labor or premature rupture of membranes). At the time of randomization (between 16 weeks, 0 days and 20 weeks, 6 days of gestation), an ultrasound examination had confirmed gestational age and no known fetal anomaly. Women were excluded for prior progesterone treatment or heparin therapy during the current pregnancy, a history of thromboembolic disease, or maternal/obstetrical complications (such as current or planned cerclage, hypertension requiring medication, or a seizure disorder).

A total of 463 pregnant women were randomized to receive either hydroxyprogesterone caproate injection (N=310) or vehicle (N=153) at a dose of 250 mg administered weekly by intramuscular injection starting between 16 weeks, 0 days and 20 weeks, 6 days of gestation, and continuing until 37 weeks of gestation or delivery. Demographics of the hydroxyprogesterone caproate injection-treated women were similar to those in the control group, and included: 59.0% Black, 25.5% Caucasian, 13.9% Hispanic and 0.6% Asian. The mean body mass index was 26.9 kg/m^2.

The proportions of women in each treatment arm who delivered at < 37 (the primary study endpoint), < 35, and < 32 weeks of gestation are displayed in Table 5.

Table 5 Proportion of Subjects Delivering at < 37, < 35 and < 32 Weeks Gestational Age (ITT Population)

Delivery Outcome | Hydroxyprogesterone Caproate Injection^1 (N=310) % | Control (N=153) % | Treatment difference and 95% Confidence Interval^2
<37 weeks | 37.1 | 54.9 | -17.8% [-28.0%, -7.4%]
<35 weeks | 21.3 | 30.7 | -9.4% [-19.0%, -0.4%]
<32 weeks | 11.9 | 19.6 | -7.7% [-16.1%, -0.3%]

^1 Four hydroxyprogesterone caproate injection-treated subjects were lost to follow-up. They were counted as deliveries at their gestational ages at time of last contact (18^4, 22^0, 34^3 and 36^4 weeks).

^2 Adjusted for interim analysis.

Compared to controls, treatment with hydroxyprogesterone caproate injection reduced the proportion of women who delivered preterm at < 37 weeks. The proportions of women delivering at < 35 and < 32 weeks also were lower among women treated with hydroxyprogesterone caproate injection. The upper bounds of the confidence intervals for the treatment difference at < 35 and < 32 weeks were close to zero. Inclusion of zero in a confidence interval would indicate the treatment difference is not statistically significant. Compared to the other gestational ages evaluated, the number of preterm births at < 32 weeks was limited.

After adjusting for time in the study, 7.5% of hydroxyprogesterone caproate injection-treated subjects delivered prior to 25 weeks compared to 4.7% of control subjects; see Figure 1.

The rates of fetal losses and neonatal deaths in each treatment arm are displayed in Table 6. Due to the higher rate of miscarriages and stillbirths in the hydroxyprogesterone caproate injection arm, there was no overall survival difference demonstrated in this clinical trial.

Table 6 Fetal Losses and Neonatal Deaths

Complication | Hydroxyprogesterone Caproate Injection N=306 A n (%) B | Control N=153 n (%) B
Miscarriages <20 weeks gestation C | 5 (2.4) | 0
Stillbirth | 6 (2.0) | 2 (1.3)
Antepartum stillbirth | 5 (1.6) | 1 (0.6)
Intrapartum stillbirth | 1 (0.3) | 1 (0.6)
Neonatal deaths | 8 (2.6) | 9 (5.9)
Total Deaths | 19 (6.2) | 11 (7.2)

A Four of the 310 hydroxyprogesterone caproate injection-treated subjects were lost to follow-up and stillbirth or neonatal status could not be determined

B Percentages are based on the number of enrolled subjects and not adjusted for time on drug

C Percentage adjusted for the number of at risk subjects (n=209 for hydroxyprogesterone caproate injection, n=107 for control) enrolled at <20 weeks gestation.

A composite neonatal morbidity/mortality index evaluated adverse outcomes in live births. It was based on the number of neonates who died or experienced respiratory distress syndrome, bronchopulmonary dysplasia, grade 3 or 4 intraventricular hemorrhage, proven sepsis, or necrotizing enterocolitis. Although the proportion of neonates who experienced 1 or more events was numerically lower in the hydroxyprogesterone caproate injection arm (11.9% vs. 17.2%), the number of adverse outcomes was limited and the difference between arms was not statistically significant.

14.2 Infant Follow-Up Safety Study

Infants born to women enrolled in this study, and who survived to be discharged from the nursery, were eligible for participation in a follow-up safety study. Of 348 eligible offspring, 79.9% enrolled: 194 children of hydroxyprogesterone caproate injection-treated women and 84 children of control subjects. The primary endpoint was the score on the Ages & Stages Questionnaire (ASQ), which evaluates communication, gross motor, fine motor, problem solving, and personal/social parameters. The proportion of children whose scores met the screening threshold for developmental delay in each developmental domain was similar for each treatment group.

16 HOW SUPPLIED/STORAGE AND HANDLING

Hydroxyprogesterone caproate injection, multi-dose vials (for intramuscular injection)

Hydroxyprogesterone caproate injection USP is supplied as 5 mL of a sterile clear yellow solution in a multi-dose glass vial.

Carton of 1 vial………………NDC 47335-037-40

Each 5 mL vial contains hydroxyprogesterone caproate USP, 250 mg/mL (25% w/v), in castor oil (28.6% v/v) and benzyl benzoate (46% v/v) with the preservative benzyl alcohol (2% v/v).

Single unit carton: Contains one 5 mL multi-dose vial of hydroxyprogesterone caproate injection (250 mg/mL) containing 1,250 mg of hydroxyprogesterone caproate.

Store at 20° to 25°C (68° to 77°F). Do not refrigerate or freeze.

Use multi-dose vials within 5 weeks after first use.

Caution: Protect vial from light. Store vial in its box. Store upright.

17 PATIENT COUNSELING INFORMATION

Advise the patient to read the FDA-approved patient labeling (Patient Information).

Counsel patients that hydroxyprogesterone caproate injection may cause pain, soreness, swelling, itching or bruising. Inform the patient to contact her physician if she notices increased discomfort over time, oozing of blood or fluid, or inflammatory reactions at the injection site [see Adverse Reactions (6.1)].

.

PATIENT INFORMATION

.

Patient Information

Hydroxyprogesterone Caproate Injection USP

(hye-DROX-ee-proe-JES-ter-one KAP-roe-ate)
vial for intramuscular use

Read this Patient Information Leaflet before you receive hydroxyprogesterone caproate injection. There may be new information. This information does not take the place of talking to your healthcare provider about your medical condition or treatment.

What is hydroxyprogesterone caproate injection?

Hydroxyprogesterone caproate injection is a prescription hormone medicine (progestin) used in women who are pregnant and who have delivered a baby too early (preterm) in the past. Hydroxyprogesterone caproate injection is used in these women to help lower the risk of having a preterm baby again. It is not known if hydroxyprogesterone caproate injection reduces the number of babies who are born with serious medical conditions or die shortly after birth. Hydroxyprogesterone caproate injection is for women who:

- Are pregnant with one baby.
- Have had a preterm delivery of one baby in the past.

Hydroxyprogesterone caproate injection is not intended for use to stop active preterm labor. It is not known if hydroxyprogesterone caproate injection is safe and effective in women who have other risk factors for preterm birth. Hydroxyprogesterone caproate injection is not for use in women under 16 years of age.

Who should not receive hydroxyprogesterone caproate injection?

Hydroxyprogesterone caproate injection should not be used if you have:

- blood clots or other blood clotting problems now or in the past
- breast cancer or other hormone-sensitive cancers now or in the past
- unusual vaginal bleeding not related to your current pregnancy
- yellowing of your skin due to liver problems during your pregnancy
- liver problems, including liver tumors
- high blood pressure that is not controlled

What should I tell my healthcare provider before receiving hydroxyprogesterone caproate injection?

Before you receive hydroxyprogesterone caproate injection, tell your healthcare provider about all of your medical conditions, including if you have:

- a history of allergic reaction to hydroxyprogesterone caproate, castor oil, or any of the other ingredients in hydroxyprogesterone caproate injection. See the end of this Patient Information leaflet for a complete list of ingredients in hydroxyprogesterone caproate injection.
- diabetes or pre-diabetes.
- epilepsy (seizures).
- migraine headaches.
- asthma.
- heart problems.
- kidney problems.
- depression.
- high blood pressure.

Tell your healthcare provider about all the medicines you take, including prescription and over-the-counter medicines, vitamins, and herbal supplements.

Hydroxyprogesterone caproate injection may affect the way other medicines work, and other medicines may affect how hydroxyprogesterone caproate injection works. Know the medicines you take. Keep a list of them to show your healthcare provider and pharmacist when you get a new medicine.
How should I receive hydroxyprogesterone caproate injection?

- Do not give yourself hydroxyprogesterone caproate injection. A healthcare provider will give you the hydroxyprogesterone caproate injection 1 time each week (every 7 days) in the upper outer area of the buttocks as an injection into the muscle (intramuscular).
- You will start receiving hydroxyprogesterone caproate injection anytime from 16 weeks and 0 days of your pregnancy, up to 20 weeks and 6 days of your pregnancy.
- You will continue to receive hydroxyprogesterone caproate injection 1 time each week until week 37 (through 36 weeks and 6 days) of your pregnancy or when your baby is delivered, whichever comes first.

What are the possible side effects of hydroxyprogesterone caproate injection?

Hydroxyprogesterone caproate injection may cause serious side effects, including:

- Blood clots. Symptoms of a blood clot may include:
- leg swelling
- redness in your leg
- a spot on your leg that is warm to the touch
- leg pain that gets worse when you bend your foot

Call your healthcare provider right away if you get any of the symptoms above during treatment with hydroxyprogesterone caproate injection.

- Allergic reactions. Symptoms of an allergic reaction may include:
- hives
- itching
- swelling of the face

Call your healthcare provider right away if you get any of the symptoms above during treatment with hydroxyprogesterone caproate injection.

- Decrease in glucose (blood sugar) tolerance. Your healthcare provider will need to monitor your blood sugar while taking hydroxyprogesterone caproate injection if you have diabetes or pre-diabetes.

- Your body may hold too much fluid (fluid retention).
- Depression.
- Yellowing of your skin and the whites of your eyes (jaundice).
- High blood pressure.

The most common side effects of hydroxyprogesterone caproate injection include:

- pain, swelling, itching or a hard bump at the injection site
- hives
- itching
- nausea
- diarrhea

Call your healthcare provider if you have the following at your injection site:

- increased pain over time
- oozing of blood or fluid
- swelling

Other side effects that may happen more often in women who receive hydroxyprogesterone caproate injection include:

- Miscarriage (pregnancy loss before 20 weeks of pregnancy)
- Stillbirth (fetal death occurring during or after the 20th week of pregnancy)
- Hospital admission for preterm labor
- Preeclampsia (high blood pressure and too much protein in your urine)
- Gestational hypertension (high blood pressure caused by pregnancy)
- Gestational diabetes
- Oligohydramnios (low amniotic fluid levels)

Tell your healthcare provider if you have any side effect that bothers you or that does not go away.
These are not all the possible side effects of hydroxyprogesterone caproate injection. For more information, ask your healthcare provider or pharmacist. Call your doctor for medical advice about side effects. You may report side effects to FDA at 1-800-FDA-1088.
How should I store hydroxyprogesterone caproate injection?

- Hydroxyprogesterone caproate injection vial for intramuscular use:
  - Store the vial at room temperature between 68°F to 77°F (20°C to 25°C).
  - Do not refrigerate or freeze.
  - Protect the vial from light.
  - Store the vial in its box in an upright position.

Keep hydroxyprogesterone caproate injection and all medicines out of the reach of children.
General information about the safe and effective use hydroxyprogesterone caproate injection.

Medicines are sometimes prescribed for purposes other than those listed in a Patient Information leaflet. Do not use hydroxyprogesterone caproate injection for a condition for which it was not prescribed. Do not give hydroxyprogesterone caproate injection to other people, even if they have the same symptoms you have. It may harm them.

This leaflet summarizes the most important information about hydroxyprogesterone caproate injection. If you would like more information, talk with your healthcare provider. You can ask your healthcare provider or pharmacist for information about hydroxyprogesterone caproate injection that is written for health professionals.
What are the ingredients in hydroxyprogesterone caproate injection?

Active ingredient: hydroxyprogesterone caproate

Inactive ingredients: castor oil, benzyl benzoate, and benzyl alcohol (a preservative)

Distributed by:

Sun Pharmaceutical Industries, Inc.

Cranbury, NJ 08512

Manufactured by:

Sun Pharmaceutical Industries Ltd.

Halol-Baroda Highway,

Halol-389 350, Gujarat, India.

For more information, call 1-800-818-4555.
Iss. 04/2019
This Patient Information has been approved by the U.S. Food and Drug Administration

PACKAGE LABEL.PRINCIPAL DISPLAY PANEL

NDC 47335-037-40
Hydroxyprogesterone Caproate Injection
1,250 mg/5 mL
(250 mg/mL)
FOR INTRAMUSCULAR USE
5 mL multidose vial
Rx only
Sterile